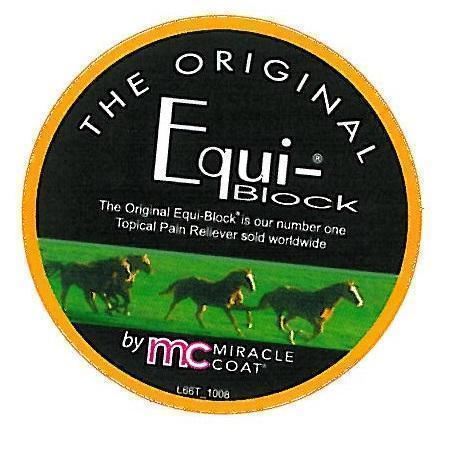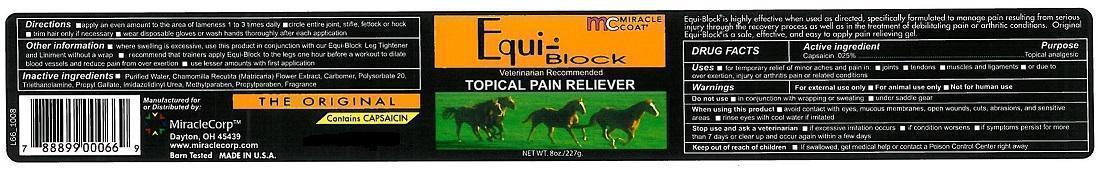 DRUG LABEL: EQUI-BLOCK
NDC: 61429-181 | Form: GEL
Manufacturer: MIRACLE CORP
Category: animal | Type: OTC ANIMAL DRUG LABEL
Date: 20200629

ACTIVE INGREDIENTS: CAPSAICIN 0.025 g/100 mL
INACTIVE INGREDIENTS: WATER; MATRICARIA CHAMOMILLA WHOLE; CARBOMER 940; POLYSORBATE 20; TROLAMINE; PROPYL GALLATE; IMIDUREA; METHYLPARABEN; PROPYLPARABEN

MIRACLE COAT - EQUI-BLOCK - THE ORIGINAL

ACTIVE INGREDIENT:

CAPSAICIN .025%

PURPOSE

TOPICAL ANALGESIC

USES

- FOR TEMPORARY RELIEF OF MINOR ACHES AND PAIN IN
- JOINTS
- TENDONS
- MUSCLES AND LIGAMENTS DUE TO OVER EXTENTION, INJURY, OR ARTHRITIS PAIN OR RELATED CONDITIONS

WARNINGS

- FOR EXTERNAL USE ONLY
- FOR ANIMAL USE ONLY
- NOT FOR HUMAN USE

DO NOT USE

- IN CONJUNCTION WITH WRAPPING OR SWEATING
- UNDER SADDLE GEAR

WHEN USING THIS PRODUCT

- AVOID CONTACT WITH EYES
- MUCOUS MEMBRANES
- OPEN WOUNDS
- CUTS
- ABRASIONS
- SENSITIVE AREAS
- RINSE EYES WITH COOL WATER IF IRRITATED

STOP USE AND CONSULT A VETERINARIAN IF

- EXCESSIVE IRRITATION OCCURS
- CONDITION WORSENS
- SYMPTOMS PERSIST FOR MORE THAN 7 DAYS OR CLEAR UP AND REOCCUR WITHIN A FEW DYS

KEEP OUT OF REACH OF CHILDREN.

- IF SWALLOWED, GET MEDICAL HELP OR CONTACT A POISON CONTROL CENTER RIGHT AWAY.

DIRECTIONS

- SHAKE WELL
- MASSAGE LIBERAL AMOUNT INTO THE REGION OF SPECIFIC PAIN OR INJURY
- CIRCLE ENTIRE JOINT WHERE APPLICABLE
- REAPPLY UP TO THREE TIMES DAILY FOR UP TO TWO WEEKS
- THEREAFTER USE ONCE DAILY OR AS NEEDED
- WEAR DISPOSABLE GLOVES OR WASH HANDS THOROUGHLY AFTER EACH APPLICATION

OTHER INFORMATION

- WHERE SWEATING IS EXCESSIVE, USE THIS PRODUCT IN CONJUNCTION WITH OUR EQUI-BLOCK LEG TIGHTENER AND LINIMENT WITHOUT A WRAP
- RECOMMEND THAT TRAINERS APPLY EQUI-BLOCK TO THE LEGS ONE HOUR BEFORE A WORKOUT TO DILATE BLOOD VESSELS AND REDUCE PAIN FROM OVER EXERTION
- USE LESSER AMOUNTS WITH FIRST APPLICATION

INACTIVE INGREDENTS

- PURIFIED WATER, CHAMOMILE EXTRACT, CARBOMER, POLYSORBATE 20, TRIETHANOLAMINE, PROPYL GALLATE, IMIDAZOLIDINYL UREA, METHYLPARABEN, PROPYLPARABEN, FRAGRANCE